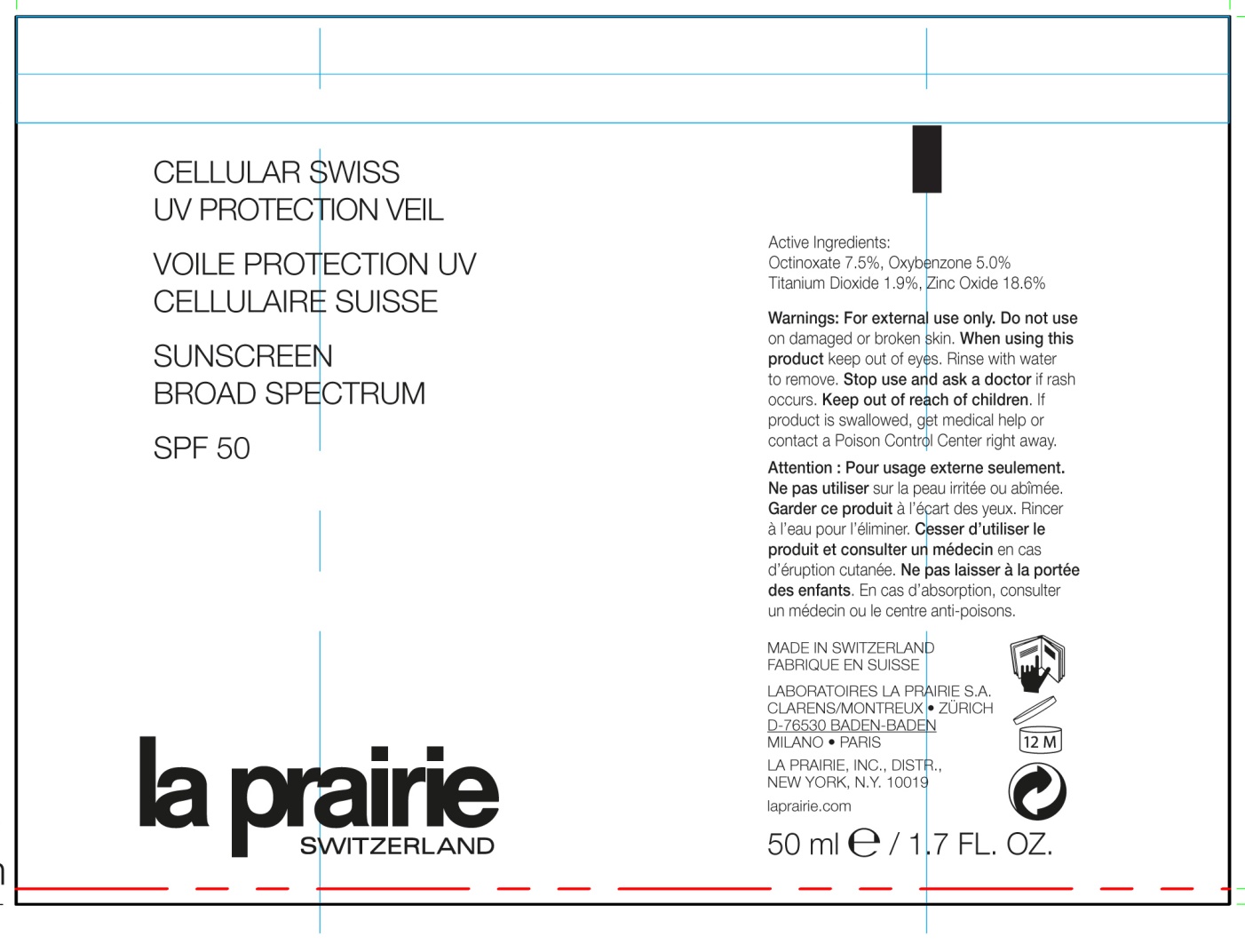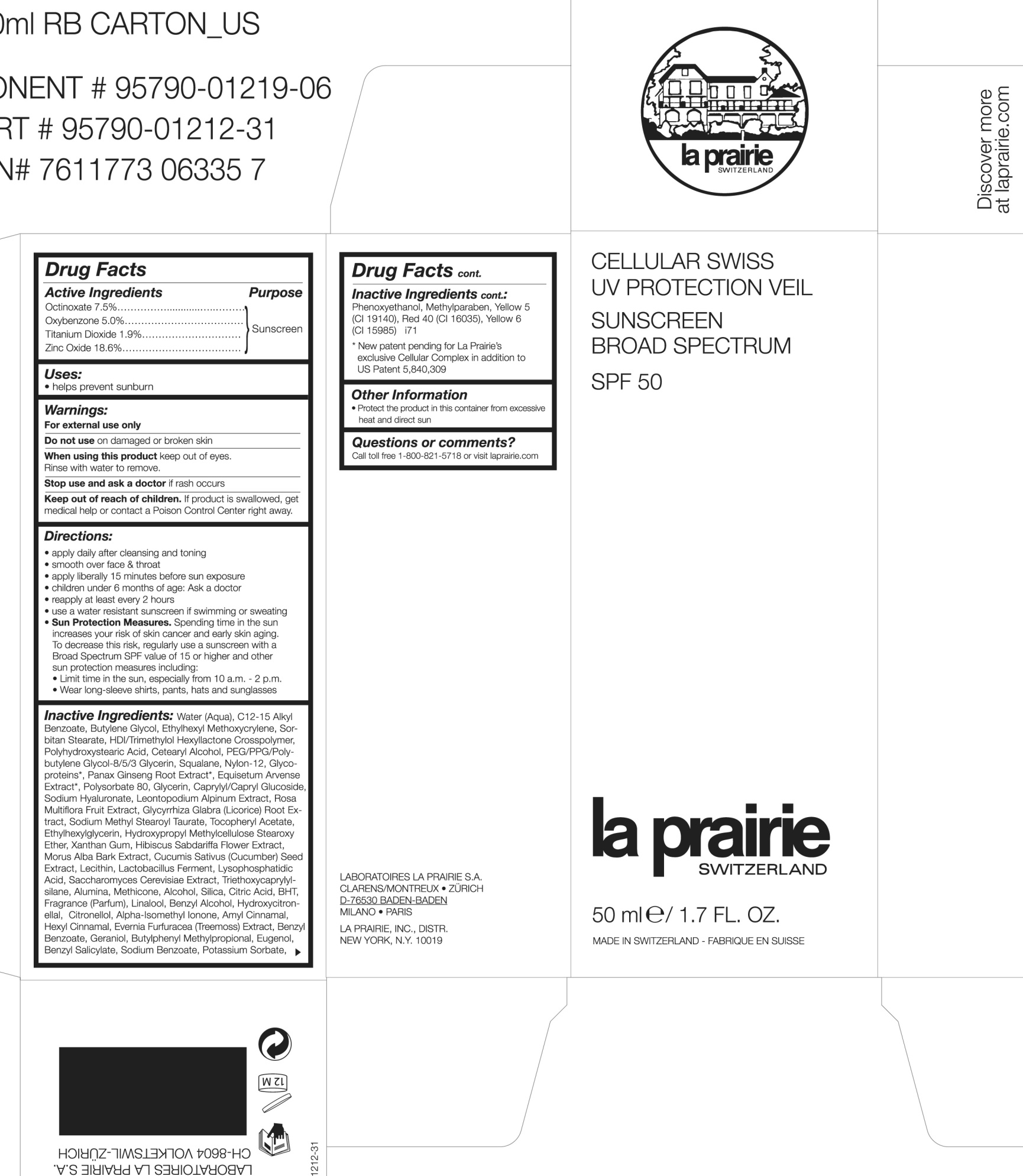 DRUG LABEL: Cellular Swiss UV Protection Veil Sunscreen Broad Spectrum SPF 50
NDC: 68807-324 | Form: CREAM
Manufacturer: Temmentec Ag
Category: otc | Type: HUMAN OTC DRUG LABEL
Date: 20170103

ACTIVE INGREDIENTS: OCTINOXATE 7.5 1/100 kg; OXYBENZONE 5 1/100 kg; TITANIUM DIOXIDE 1.9 1/100 kg; ZINC OXIDE 18.6 1/100 kg
INACTIVE INGREDIENTS: WATER; ALKYL (C12-15) BENZOATE; BUTYLENE GLYCOL; ETHYLHEXYL METHOXYCRYLENE; SORBITAN MONOSTEARATE; HEXAMETHYLENE DIISOCYANATE/TRIMETHYLOL HEXYLLACTONE CROSSPOLYMER; POLYHYDROXYSTEARIC ACID (2300 MW); CETOSTEARYL ALCOHOL; SQUALANE; NYLON-12; GLYCOPROTEIN HORMONES ALPHA CHAIN; ASIAN GINSENG; EQUISETUM ARVENSE BRANCH; POLYSORBATE 80; GLYCERIN; CAPRYLYL/CAPRYL OLIGOGLUCOSIDE; HYALURONATE SODIUM; LEONTOPODIUM NIVALE SUBSP. ALPINUM FLOWER; ROSA MULTIFLORA FRUIT; LICORICE; SODIUM METHYL STEAROYL TAURATE; ALPHA-TOCOPHEROL ACETATE; ETHYLHEXYLGLYCERIN; XANTHAN GUM; HIBISCUS SABDARIFFA FLOWER; MORUS ALBA BARK; CUCUMBER SEED; LECITHIN, SOYBEAN; LACTOBACILLUS REUTERI; SACCHAROMYCES CEREVISIAE; TRIETHOXYCAPRYLYLSILANE; ALUMINUM OXIDE; METHICONE (20 CST); ALCOHOL; SILICON DIOXIDE; CITRIC ACID MONOHYDRATE; BUTYLATED HYDROXYTOLUENE; LINALOOL, (+)-; BENZYL ALCOHOL; HYDROXYCITRONELLAL; .BETA.-CITRONELLOL, (R)-; ISOMETHYL-.ALPHA.-IONONE; .ALPHA.-AMYLCINNAMALDEHYDE; .ALPHA.-HEXYLCINNAMALDEHYDE; PSEUDEVERNIA FURFURACEA; BENZYL BENZOATE; GERANIOL; BUTYLPHENYL METHYLPROPIONAL; EUGENOL; BENZYL SALICYLATE; SODIUM BENZOATE; POTASSIUM SORBATE; PHENOXYETHANOL; METHYLPARABEN; FD&C YELLOW NO. 5; FD&C RED NO. 40; FD&C YELLOW NO. 6

Cellular Swiss UV Protector Veil Sunscreen Broad Spectrum SPF 50

Active ingredients Purpose

Octinoxate 7.5% Sunscreen

Oxybenzone 5.0% Sunscreen

Titanium Dioxide 1.9% Sunscreen

Zinc Oxide18.6% Sunscreen

PURPOSE

helps prevent sunburn

Keep out of reach of children. If product is swallowed, get medical help or contact a Poison Control Center right away

Stop use and ask a doctor if rash occurs.

Warnings:

For external use only

Do not use on damaged or broken Skin

When using this product keep out of eyes

Rinse with water to remove

Directions

apply daily after cleansing and toning

smooth over face & throat

apply liberally 15 minutes before sun exposure

children under 6 months of age: Ask a doctor

reapply at least every 2 hours

use a water resistant sunscreen if swimming or sweating

Sun Protection Measures. Spending time in the sun increases your risk of skin cancer and early skin aging. To decrease this risk regularly use a sunscreen with a Broad Spectrum SPF value of 15 or higher and other sun protection measures including:

Limit time in the sun, especially from 10 a.m. - 2p.m.

Wear long sleeve shirts, pants, hats and sunglasses

INACTIVE INGREDIENT

Inactive ingredients: Water(Aqua), C12-15 Alkyl Benzoate, Butylene Glycol, Ethylhexyl Methoxycrylene, Sorbitan Stearate, HDI/Trimethylol Hexylactone Crosspolymer, Polyhydroxystearic Acid, Cetearyl Alcohol, PEG/PPG/Polybutene Glycol-8/5/3 Glycerin, Squalane, Nylon-12, Glycolproteins, Panax Ginseng Root extract, Equisetum Arvense Extract, Polysorbate 80, Glycerin, Caprylyl/Capryl Glucoside, Sodium Hyaluronate, Leontopdodium Alpinum Extract, Rosa multifora Fruit Extract, Glycyrrhiza Glabra (licorice) Root Extract, Sodium Methyl Stearoyl Taurate, Tocopheryl Acetate, Ethylhexyglycerin, Hydroxypropyl Methylcellulose Stearoxy Ether, Xanthan Gum, Hibiscus Sabdariffa Flower Extract, Morus Alba Bark Extract, Cucumis Sativus (cucumber) seed Extract, Lecithin, Lactobacillus Ferment, Lysophosphatidic Acid, Sacharomyces Cerevisiae Extract, Triethoxycaprylylsilane, Alumina, Methicone, Alcohol, Silica, Citric Acid, BHT, Fragrance (parfum) Linalool, Benzyl Alcohol, Hydroxycitronellal, Citronellol, Alpa-isomethyl ionone, Amyl Cinnamal, Hexyl Cinnamal, Evernia Furfuracea (Treemoss) Extract, Benzyl Benzoate, Geraniolm Butylphenyl Methylpropional, Eugenol, Benzyl Salicylate, Sodium Benzoate, Potassium Sorbate, Phenoxyethanol, Methylparaben, Yellow 5 (CI 19140), Red 40 (CI16035), Yellow 6 (CI 15985)

PACKAGE LABEL

Cellular Swiss UV Protection Veil

Sunscreen Broad Spectrum SPF 50

La Prairie Switzerland

50 ml/ 1.7 FL. OZ.